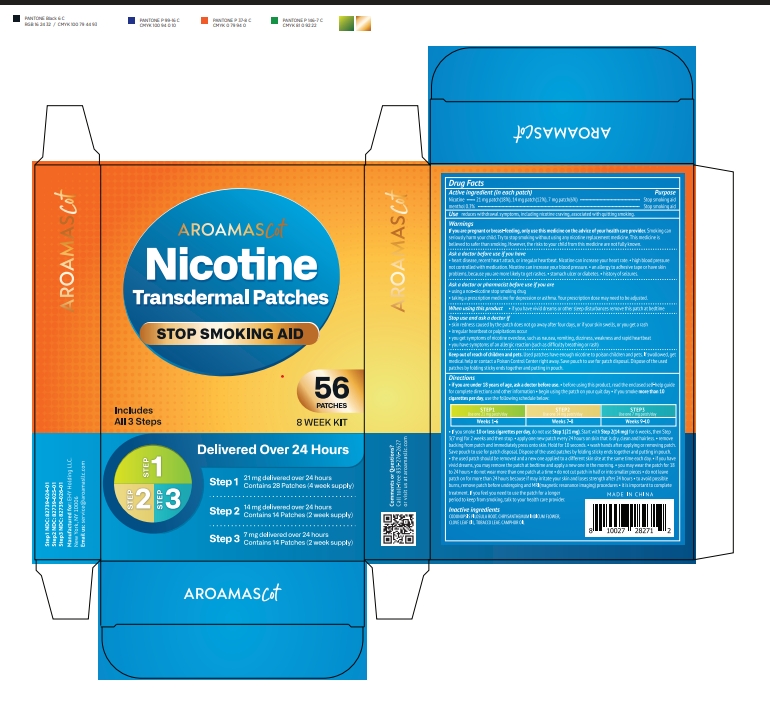 DRUG LABEL: Aroamas Cot Nicotine Transdermal Patches Kit
NDC: 85831-032 | Form: PATCH
Manufacturer: PCHEERY LLC
Category: otc | Type: HUMAN OTC DRUG LABEL
Date: 20250624

ACTIVE INGREDIENTS: MENTHOL 0.3 g/100 1; NICOTINE 18 g/100 1
INACTIVE INGREDIENTS: CHRYSANTHEMUM INDICUM FLOWER; CLOVE LEAF OIL; CAMPHOR OIL; CODONOPSIS PILOSULA ROOT; TOBACCO LEAF

Initial Drug Listing - Aroamas Cot Patch Kit

ACTIVE INGREDIENT

Nicotine 21mg, 14mg, 7mg

menthol 0.3%

PURPOSE

Stop smoking aid

INDICATIONS AND USAGE

reduces withdrawal symptoms, including nicotine craving, associated with quitting smoking.

WARNINGS

If you are pregnant or breast-feeding, only use this medicine on the advice of your health care provider. Smoking can seriously harm your child. Try to stop smoking without using any nicotine replacement medicine. This medicine is believed to be safer than smoking. However, the risks to your child from this medicine are not fully known.

ASK DOCTOR

- heart disease, recent heart attack, or irregular heartbeat. Nicotine can increase your heart rate.
- high blood pressure not controlled with medication. Nicotine can increase your blood pressure.
- an allergy to adhesive tape or have skin problems, because you are more likely to get rashes.
- stomach ulcer or diabetes.
- history of seizures.

ASK DOCTOR/PHARMACIST

- using a non-nicotine stop smoking drug
- taking a prescription medicine for depression or asthma. Your prescription dose may need to be adjusted.

WHEN USING

- if you have vivid dreams or other sleep disturbances remove this patch at bedtime.

STOP USE

- skin redness caused by the patch does not go away after four days, or if your skin swells, or you get a rash.
- irregular heartbeat or palpitations occur.
- you get symptoms of nicotine overdose, such as nausea, vomiting, dizziness, weakness and rapid heartbeat.
- you have symptoms of an allergic reaction (such as difficulty breathing or rash)

KEEP OUT OF REACH OF CHILDREN

Used patches have enough nicotine to poison children and pets. If swallowed, get medical help or contact a Poison Control Center right away. Save pouch to use for patch disposal. Dispose of the used patches by folding sticky ends together and putting in pouch.

DOSAGE AND ADMINISTRATION

- if you are under 18 years of age, ask a doctor before use.
- before using this product, read the enclosed self-help guide for complete directions and other information
- begin using the patch on your quit day
- if you somke more than 10 cigarettes per day, use the following schedule below:

STEP 1
Use one 21 mg patch/day
Weeks 1-6
STEP 2
Use one 14 mg patch/day
Weeks 7-8
STEP 3
Use one 7 mg patch/day
Weeks 9-10

- if you smoke 10 or less cigarettes per day, do not use Step 1(21mg), start with Step 2(14mg) for 6 weeks, then Step 3(7mg) for 2 weeks and then stop.
- apply one new patch every 24 hours on skin that is dry, clean and hairless.
- remove backing from patch and immediately press onto skin. Hold for 10 seconds.
- wash hands after applying or removing patch. Save pouch to use for patch disposal. Dispose of the used patches by folding sticky ends together and putting in pouch.
- the used patch should be removed and a new one applied to a different skin site at the same time each day.
- if you have vivid dreams, you may remove the patch at bedtime and apply a new one in the morning.
- you may wear the patch for 18-24 hours.
- do not wear more than one patch at a time
- do not cut patch in half or into smaller pieces
- do not leave patch on for more than 24 hours because it may irritate your skin and loses strength after 24 hours
- to avoid possible burns, remove patch before undergoing any MRI (magnetic resonance imaging) procedures
- It is important to complete treatment. If you feel you need to use the patch for a longer period to keep from smoking, talk to your health care provider.

INACTIVE INGREDIENT

CODONOPSIS PILOSULA ROOT, CHRYSANTHEMUM INDICUM FLOWER, CLOVE LEAF OIL, TOBACCO LEAF, CAMPHOR OIL

TROUBLESHOOTING

Comments or Questions? Call toll-free: 833-276-2627 - Or visit us at aroamascot.com